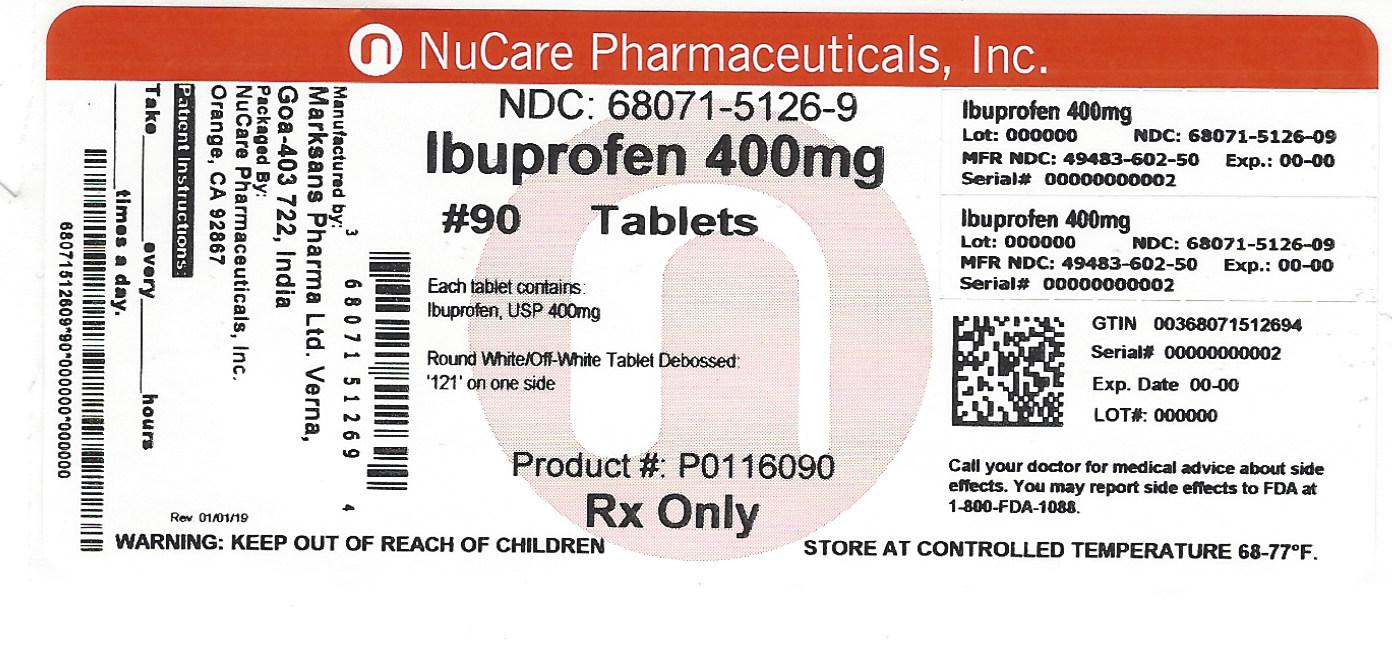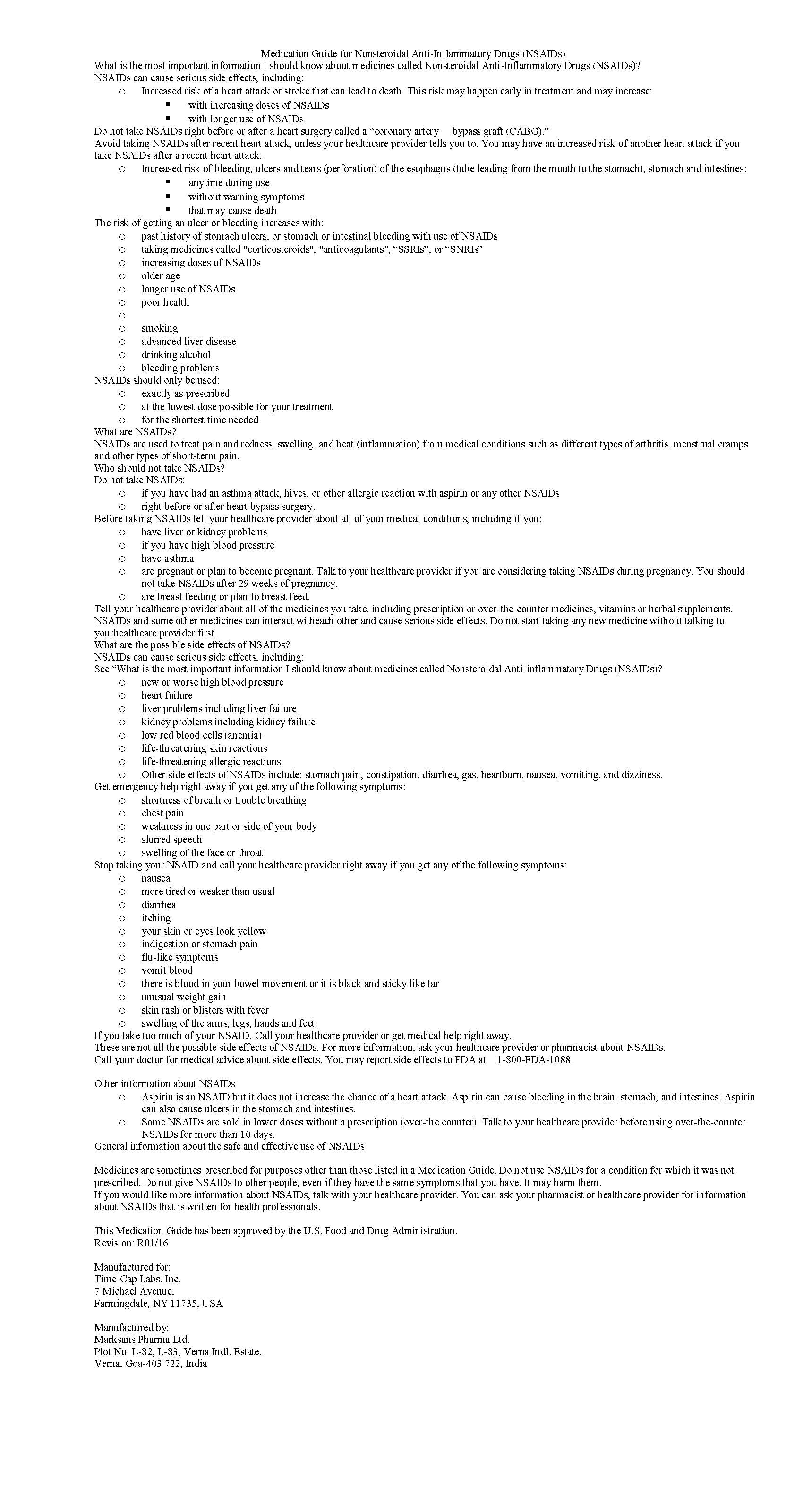 DRUG LABEL: IBUPROFEN
NDC: 68071-5126 | Form: TABLET, FILM COATED
Manufacturer: NuCare Pharmaceuticals,Inc.
Category: prescription | Type: HUMAN PRESCRIPTION DRUG LABEL
Date: 20240620

ACTIVE INGREDIENTS: IBUPROFEN 400 mg/1 1
INACTIVE INGREDIENTS: SILICON DIOXIDE; CROSCARMELLOSE SODIUM; MAGNESIUM STEARATE; CELLULOSE, MICROCRYSTALLINE; POLYETHYLENE GLYCOL, UNSPECIFIED; POLYVINYL ALCOHOL; STARCH, PREGELATINIZED CORN; TALC; TITANIUM DIOXIDE

IBUPROFEN 400 MG - 600 MG AND 800 MG TABLETS

HOW SUPPLIED

400mg (white to of white, round, biconvex, film coated tablets debossed with 121 on one side and plain on the other side)

NDC 68071-5126-3 BOTTLES OF 30

NDC 68071-5126-9 BOTTLES OF 90